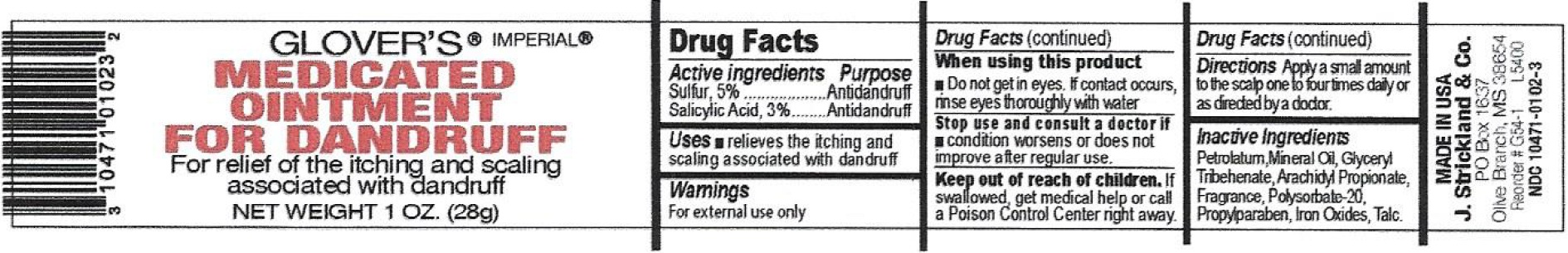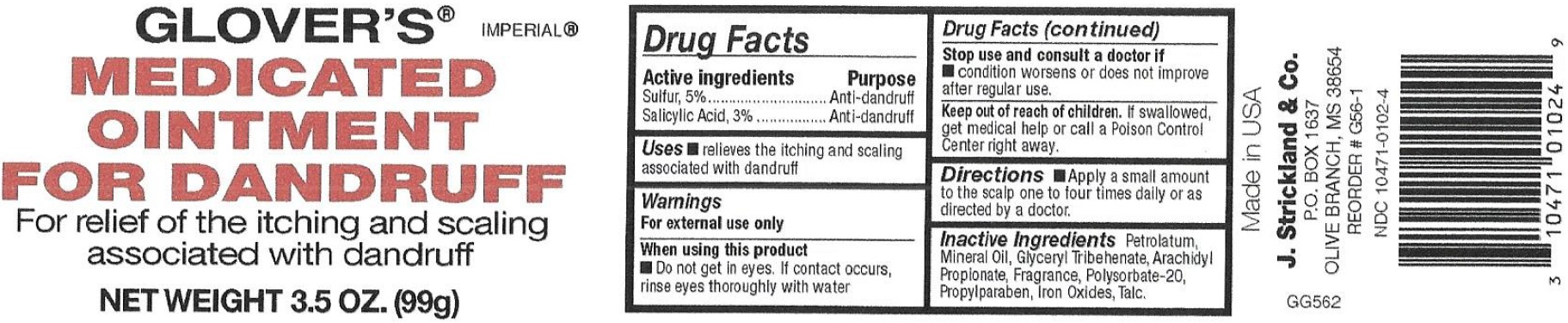 DRUG LABEL: Glovers Anti-Dandruff
NDC: 12022-009 | Form: OINTMENT
Manufacturer: J. Strickland & Co.
Category: otc | Type: HUMAN OTC DRUG LABEL
Date: 20231021

ACTIVE INGREDIENTS: SULFUR 50 mg/1 g; SALICYLIC ACID 30 mg/1 g
INACTIVE INGREDIENTS: PETROLATUM; MINERAL OIL; TRIBEHENIN; ARACHIDYL PROPIONATE; POLYSORBATE 20; PROPYLPARABEN; FERRIC OXIDE RED; TALC

Glover's Anti-Dandruff Ointment

Active ingredients

Sulfur, 5%

Salicylic Acid, 3%

Purpose

Antidandruff

Antidandruff

Uses

- relieves the itching and scaling associated with dandruff

Warnings

For external use only

When using this product

- Do not get in eyes. If contact occurs, rinse eyes thoroughly with water

Stop use and consult a doctor if

- condition worsens or does not improve after regular use.

Keep out of reach of children

If swallowed, get medical help or call a Poison Control Center right away.

Directions

Apply a small amount to the scalp one to four times daily or as directed by a doctor

Inactive Ingredients

Petrolatum, Mineral Oil, Glyceryl Tribehenate, Arachidyl Propionate, Fragrance, Polysorbate-20, Propylparaben, Iron Oxides, Talc.